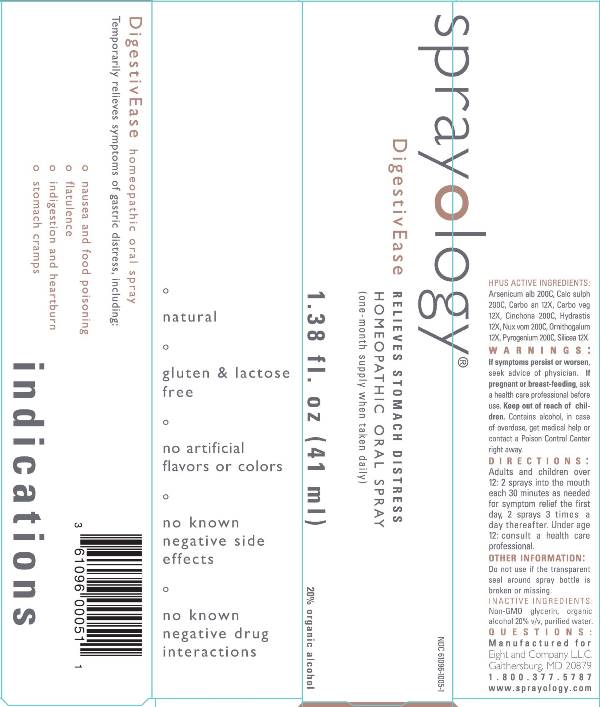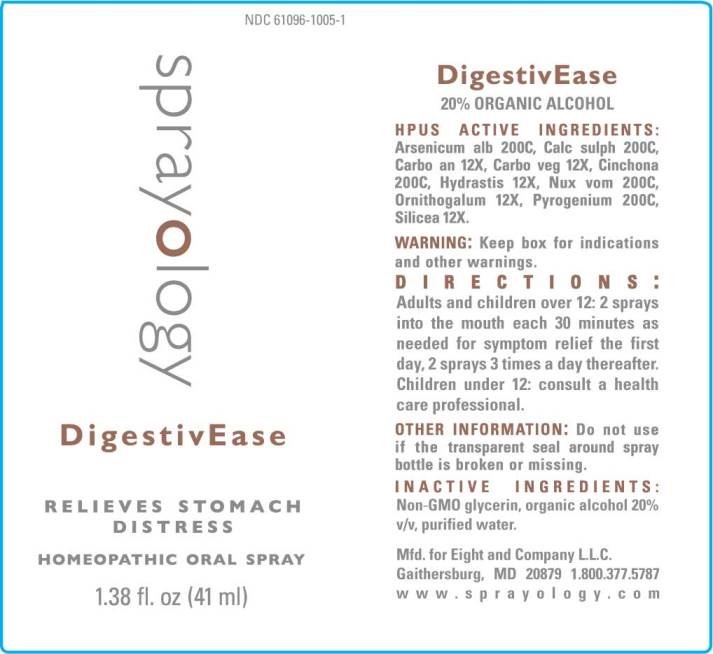 DRUG LABEL: DigestivEase
NDC: 61096-1005 | Form: LIQUID
Manufacturer: Eight and Company L.L.C
Category: homeopathic | Type: HUMAN OTC DRUG LABEL
Date: 20251217

ACTIVE INGREDIENTS: ARSENIC TRIOXIDE 200 [hp_C]/41 mL; CALCIUM SULFATE ANHYDROUS 200 [hp_C]/41 mL; CARBO ANIMALIS 12 [hp_X]/41 mL; ACTIVATED CHARCOAL 12 [hp_X]/41 mL; CINCHONA OFFICINALIS BARK 200 [hp_C]/41 mL; GOLDENSEAL 12 [hp_X]/41 mL; STRYCHNOS NUX-VOMICA SEED 200 [hp_C]/41 mL; ORNITHOGALUM UMBELLATUM WHOLE 12 [hp_X]/41 mL; RANCID BEEF 200 [hp_C]/41 mL; SILICON DIOXIDE 12 [hp_X]/41 mL
INACTIVE INGREDIENTS: GLYCERIN; ALCOHOL; WATER

DigestivEase

ACTIVE INGREDIENTS:

Arsenicum alb 200C, Calc sulph 200C, Carbo an 12X, Carbo veg 12X, Cinchona 200C, Hydrastis 12X, Nox vomica 200C, Ornithogalum 12X, Pyrogenium 200, Silicea 12X.

PURPOSE:

Temporarily relieves symptoms of gastric distress, including:

° nausea and food poisoning
° flatulence
° indigestion and heartburn
° stomach cramps

WARNINGS:

Keep box for indications and other warnings.

If symptoms persist or worsen, seek advice of physician. If pregnant or breast-feeding, ask a health care professional before use.

Keep out of reach of children. Contains alcohol, in case of overdose, get medical help or contact a Poison Control Center right away.

Keep out of reach of children. Contains alcohol, in case of overdose, get medical help or contact a Poison Control Center right away.

DIRECTIONS:

Adults and children over 12: 2 sprays into the mouth each 30 minutes as needed for symptom relief the first day, 2 sprays 3 times a day thereafter. Under age 12 consult a health care professional.

OTHER INFORMATION:

Do not use if the transparent seal around spray bottle is broken or missing.

INDICATIONS:

Temporarily relieves symptoms of gastric distress, including:

° nausea and food poisoning

° flatulence

° indigestion and heartburn

° stomach cramps

° natural

° gluten & lactose free

° no artificial flavors or colors

° no known negative side effects

° no known negative drug interactions

INACTIVE INGREDIENTS:

Non-GMO glycerin, organic alcohol 20% v/v, purified water.

QUESTIONS:

Mfd. for Eight and Company L.L.C.

Gaithersburg, MD 20879 1.800.377.5787

www.sprayology.com

PACKAGE LABEL DISPLAY:

Sprayology

DigestivEase

RELIEVES STOMACH DISTRESS

HOMEOPATHIC ORAL SPRAY

1.38 fl. oz (41 ml)